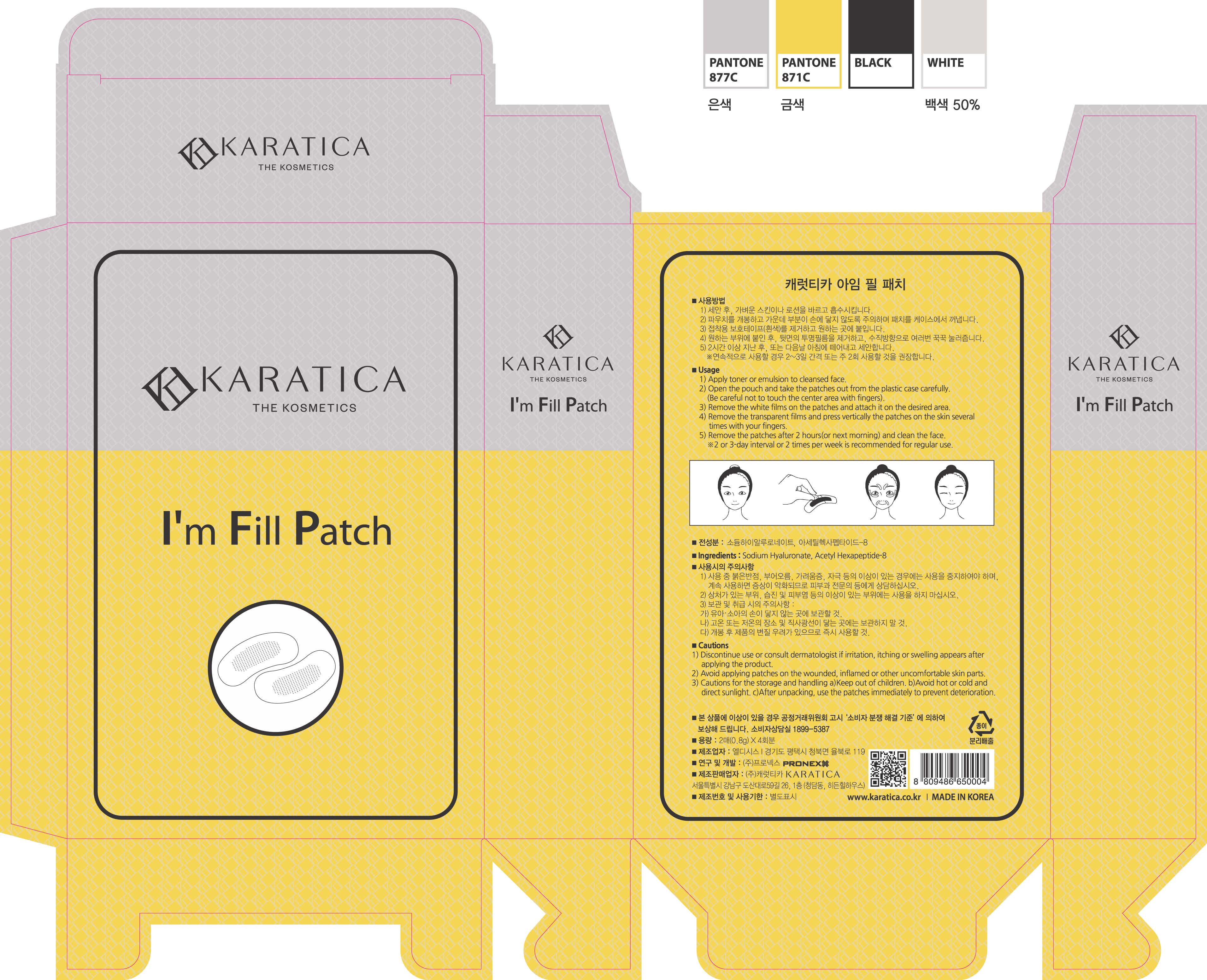 DRUG LABEL: Im Fill
NDC: 70514-0009 | Form: PATCH
Manufacturer: Karatica Co., Ltd
Category: otc | Type: HUMAN OTC DRUG LABEL
Date: 20171207

ACTIVE INGREDIENTS: HYALURONATE SODIUM 99.97 g/100 g
INACTIVE INGREDIENTS: ACETYL HEXAPEPTIDE-8

ACTIVE INGREDIENT

Sodium Hyaluronate

INACTIVE INGREDIENT

Acetyl Hexapeptide-8

PURPOSE

Multi Function - Anti-Wrinkle Moisturizing

keep out or reach of the children

INDICATIONS AND USAGE

1) Apply toner or emulsion to cleansed face.

2) Open the pouch and take the patches out from the plastic case carefully.

(Be careful not to touch the center area with fingers.)

3) Remove the white films on the patches and attach it on the desired area.

4) Remove the transparent films and press vertically the patches on the skin several times with your fingers.

5) Remove the patches after 2 hours (or next morning) and clean the face.

*2 or 3 day interval or 2 times per week is recommended for regular use.

WARNINGS

1) Discontinue use or consult dermatologist if irritation, itching or swelling appears after applying the product.

2) Avoid applying patches on the wounded, inflamed or other uncomfortable skin part.

3) Cautions for the storage and handling a) Keep out of children. B) Avoid hot or cold and direct sunlight. c) After unpacking, use the patches immediately to prevent deterioration.

DOSAGE AND ADMINISTRATION

for external use only